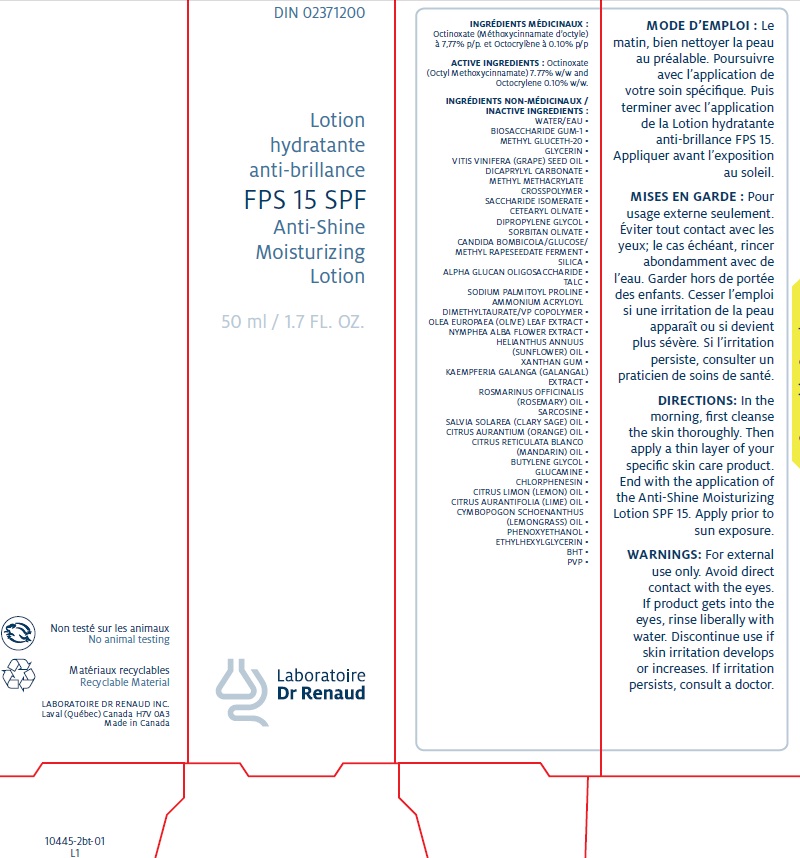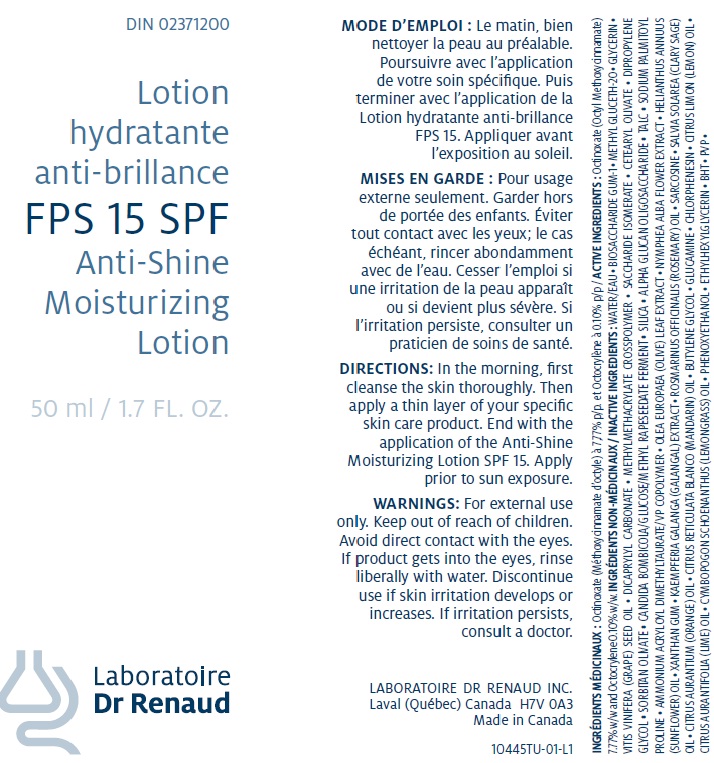 DRUG LABEL: SPF 15 Anti-shine moisturizing
NDC: 62499-445 | Form: LOTION
Manufacturer: Laboratoire Dr Renaud Inc.
Category: otc | Type: HUMAN OTC DRUG LABEL
Date: 20111129

ACTIVE INGREDIENTS: OCTINOXATE 7.77 g/100 g; OCTOCRYLENE 0.1 g/100 g
INACTIVE INGREDIENTS: WATER ; BIOSACCHARIDE GUM-1; GLYCERIN; METHYL GLUCETH-20    ; GRAPE SEED OIL    ; DICAPRYLYL CARBONATE    ; METHYL METHACRYLATE; SACCHARIDE ISOMERATE    ; CETEARYL OLIVATE    ; DIPROPYLENE GLYCOL    ; SORBITAN OLIVATE; SILICON DIOXIDE ; .ALPHA.-GLUCAN OLIGOSACCHARIDE; TALC; SODIUM PALMITOYL PROLINE; BUTYLENE GLYCOL; GLUCAMINE; OLEA EUROPAEA LEAF; NYMPHAEA ALBA FLOWER; SUNFLOWER OIL; POVIDONE K30; LESSER GALANGAL ROOT; ROSEMARY OIL; SARCOSINE; CLARY SAGE OIL; BUTYLATED HYDROXYTOLUENE; ORANGE OIL; MANDARIN OIL; CHLORPHENESIN; LEMON OIL; LIME OIL; WEST INDIAN LEMONGRASS OIL; PHENOXYETHANOL; ETHYLHEXYLGLYCERIN; XANTHAN GUM; AMMONIUM ACRYLOYLDIMETHYLTAURATE/VP COPOLYMER

Drug Facts

Active Ingredients

Octinoxate (Octyl Methoxycinnamate) 7.77% w/w and Octocrylene 0.10% w/w

INACTIVE INGREDIENTS

WATER/EAU • BIOSACCHARIDE GUM-1 • METHYL GLUCETH-20 • GLYCERIN •VITIS VINIFERA (GRAPE) SEED OIL • DICAPRYLYL CARBONATE • METHYLMETHACRYLATE CROSSPOLYMER • SACCHARIDE ISOMERATE • CETEARYL OLIVATE • DIPROPYLENE GLYCOL • SORBITAN OLIVATE • CANDIDA BOMBICOLA/GLUCOSE/METHYL RAPESEEDATE FERMENT • SILICA • ALPHA GLUCAN OLIGOSACCHARIDE • TALC • SODIUM PALMITOYL PROLINE • AMMONIUM ACRYLOYL DIMETHYLTAURATE/VP COPOLYMER • OLEA EUROPAEA (OLIVE) LEAF EXTRACT • NYMPHEA ALBA FLOWER EXTRACT • HELIANTHUS ANNUUS (SUNFLOWER) OIL • XANTHAN GUM • KAEMPFERIA GALANGA (GALANGAL) EXTRACT • ROSMARINUS OFFICINALIS (ROSEMARY) OIL • SARCOSINE • SALVIA SOLAREA (CLARY SAGE) OIL • CITRUS AURANTIUM (ORANGE) OIL • CITRUS RETICULATA BLANCO (MANDARIN) OIL • BUTYLENE GLYCOL • GLUCAMINE • CHLORPHENESIN • CITRUS LIMON (LEMON) OIL • CITRUS AURANTIFOLIA (LIME) OIL • CYMBOPOGON SCHOENANTHUS (LEMONGRASS) OIL • PHENOXYETHANOL • ETHYLHEXYLGLYCERIN • BHT • PVP •

DOSAGE AND ADMINISTRATION

In the morning, first cleanse the skin thoroughly. Then apply a thin layer of your specific skin care product. End with the application of the Anti-Shine Moisturizing Lotion SPF 15. Apply prior to sun exposure.

WARNINGS

For external use only. Keep out of reach of children. Avoid direct contact with the eyes. If product gets into the eyes, rinse liberally with water. Discontinue use if skin irritation develops or increases. If irritation persists, consult a doctor.

image of tube 50 ml label

image of carton 50ml label